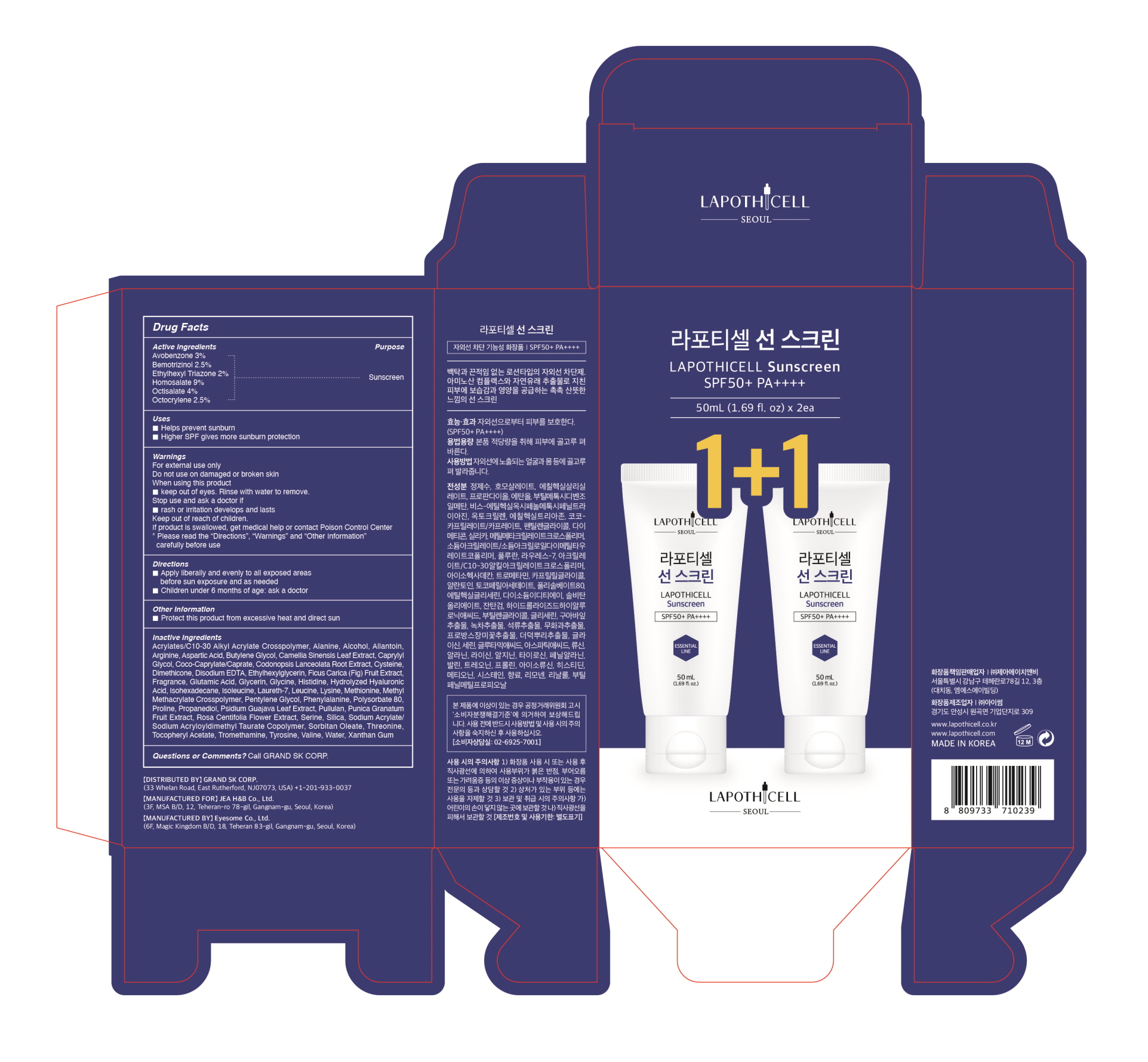 DRUG LABEL: LAPOTHICELL Sunscreen
NDC: 58832-0005 | Form: CREAM
Manufacturer: EYESOME. Co.,Ltd.
Category: otc | Type: HUMAN OTC DRUG LABEL
Date: 20200825

ACTIVE INGREDIENTS: HOMOSALATE 4.5 g/50 mL; OCTISALATE 2 g/50 mL; AVOBENZONE 1.5 g/50 mL; BEMOTRIZINOL 1.75 g/50 mL; OCTOCRYLENE 1.75 g/50 mL; ETHYLHEXYL TRIAZONE 1 g/50 mL
INACTIVE INGREDIENTS: WATER; ALCOHOL; DIMETHICONE; CAPRYLYL GLYCOL; ALLANTOIN; POLYSORBATE 80; BUTYLENE GLYCOL; GLYCERIN

ACTIVE INGREDIENT

Avobenzone, Bemotrizinol, Ethylhexyl Triazone, Homosalate, Octisalate, Octocrylene

PURPOSE

Helps prevent sunburn.

Higher SPF gives more sunburn protection.

DOSAGE AND ADMINISTRATION

For topical use only

WARNINGS

For external use only

Do not use on damaged or broken skin

When using this product

*Keep out of eyes. Rinse with water to remove.

Stop use and ask a doctor if

*rash or irritation develops and lasts

Keep our of reach of children.

If product is swallowed, get medical help or contact Poison Control Center

*Please read the "Directions", "Warnings", and "Other Information" carefully before use

Keep out of reach of children.

If product is swallowed, get medical

Help or contact a poison Control Center right away.

INDICATIONS AND USAGE

Apply liberally and evenly to all exposed areas before sun exposure and as needed

Children under 6 months of age: ask a doctor

INACTIVE INGREDIENT

Water, Propanediol, Alcohol, Coco-Caprylate/Caprate, Pentylene Glycol, Dimethicone, Silica, Methyl Methacrylate Crosspolymer, Sodium Acrylate/Sodium Acryloyldimethyl Taurate Copolymer, Pullulan, Laureth-7, Acrylates/C10-30 Alkyl Acrylate Crosspolymer, Isohexadecane, Tromethamine, Caprylyl Glycol, Allantoin, Tocopheryl Acetate, Polysorbate 80, Ethylhexylglycerin, Disodium EDTA, Sorbitan Oleate, Xanthan Gum, Hydrolyzed Hyaluronic Acid, Butylene Glycol, Glycerin, Psidium Guajava Leaf Extract, Camellia Sinensis Leaf Extract, Punica Granatum Fruit Extract, Ficus Carica (Fig) Fruit Extract, Rosa Centifolia Flower Extract, Codonopsis Lanceolata Root Extract, Glycine, Serine, Glutamic Acid, Aspartic Acid, Leucine, Alanine, Lysine, Arginine, Tyrosine, Phenylalanine, Valine, Threonine, Proline, Isoleucine, Histidine, Methionine, Cysteine, Fragrance, Limonene, Linalool, Butylphenyl Methylpropional